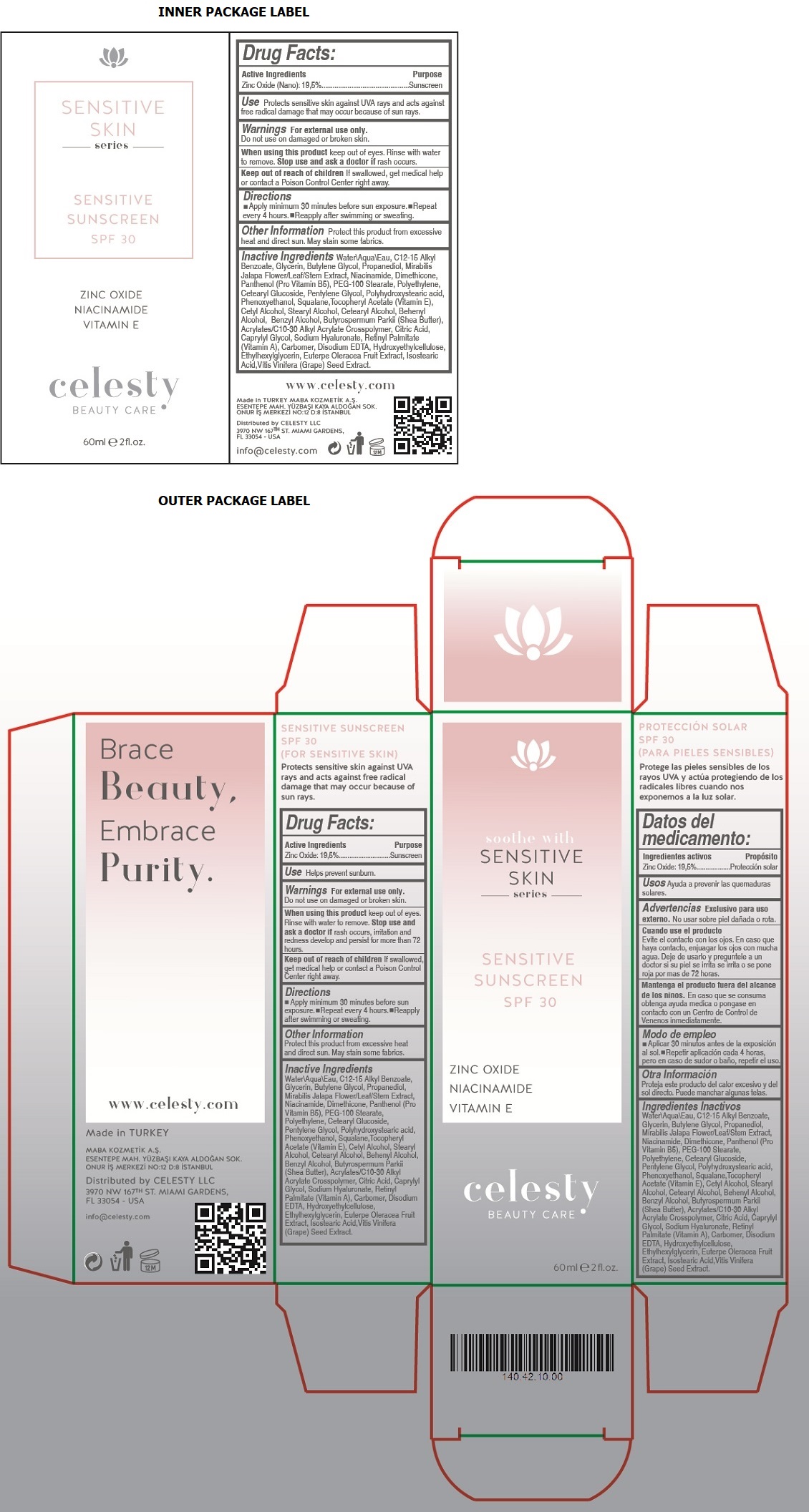 DRUG LABEL: Celesty
NDC: 81120-111 | Form: LOTION
Manufacturer: MABA KOZMETIK LIMITED SIRKETI
Category: otc | Type: HUMAN OTC DRUG LABEL
Date: 20201214

ACTIVE INGREDIENTS: ZINC OXIDE 195 mg/1 mL
INACTIVE INGREDIENTS: WATER; ALKYL (C12-15) BENZOATE; GLYCERIN; BUTYLENE GLYCOL; PROPANEDIOL; MIRABILIS JALAPA FLOWERING TOP; NIACINAMIDE; DIMETHICONE; DEXPANTHENOL; PEG-100 STEARATE; HIGH DENSITY POLYETHYLENE; CETEARYL GLUCOSIDE; PENTYLENE GLYCOL; POLYHYDROXYSTEARIC ACID (2300 MW); PHENOXYETHANOL; SQUALANE; .ALPHA.-TOCOPHEROL ACETATE; CETYL ALCOHOL; STEARYL ALCOHOL; CETOSTEARYL ALCOHOL; DOCOSANOL; BENZYL ALCOHOL; SHEA BUTTER; CARBOMER INTERPOLYMER TYPE A (ALLYL SUCROSE CROSSLINKED); CITRIC ACID MONOHYDRATE; CAPRYLYL GLYCOL; HYALURONATE SODIUM; VITAMIN A PALMITATE; CARBOMER HOMOPOLYMER, UNSPECIFIED TYPE; EDETATE DISODIUM ANHYDROUS; HYDROXYETHYL CELLULOSE, UNSPECIFIED; ETHYLHEXYLGLYCERIN; ACAI; ISOSTEARIC ACID; VITIS VINIFERA SEED

Celesty SENSITIVE SKIN series SUNSCREEN SPF 30

Active Ingredients

Zinc Oxide: 19,5%

Purpose

Sunscreen

Use

Helps prevent sunburn.

Warnings

For external use only. Do not use on damaged or broken skin.

When using this product keep out of eyes. Rinse with water to remove.

Stop use and ask a doctor if rash occurs, irritation and redness develop and persist for more than 72 hours.

Keep out of reach of children If swallowed, get medical help or contact a Poison Control Center right away.

Directions

• Apply minimum 30 minutes before sun exposure. • Repeat every 4 hours • Reapply after swimming or sweating.

Other Information

Protect this product from excessive heat and direct sun. May stain some fabrics.

Inactive Ingredients

Water\Aqua\Eau, C12-15 Alkyl Benzoate, Glycerin, Butylene Glycol, Propanediol, Mirabilis Jalapa Flower/Leaf/Stem Extract, Niacinamide, Dimethicone, Panthenol (Pro Vitamin B5), PEG-100 Stearate, Polyethylene, Cetearyl Glucoside, Pentylene Glycol, Polyhydroxystearic acid, Phenoxyethanol, Squalane, Tocopheryl Acetate (Vitamin E), Cetyl Alcohol, Stearyl Alcohol, Cetearyl Alcohol, Behenyl Alcohol, Benzyl Alcohol, Butyrospermum Parkii (Shea Butter), Acrylates/C10-30 Alkyl Acrylate Crosspolymer, Citric Acid, Caprylyl Glycol, Sodium Hyaluronate, Retinyl Palmitate (Vitamin A), Carbomer, Disodium EDTA, Hydroxyethylcellulose, Ethylhexylglycerin, Euterpe Oleracea Fruit Extract, Isostearic Acid, Vitis Vinifera (Grape) Seed Extract.

soothe with SENSITIVE SKIN series

ZINC OXIDE

NIACINAMIDE

VITAMIN E

BEAUTY CARE

Brace Beauty, Embrace Purity.

www.celesty.com

Made in TURKEY

MABA KOZMETIK A.S.

ESENTEPE MAH. YUZBASI KAYA ALDOGAN SOK.

ONUR IS MERKEZI NO:12 D:8 ISTANBUL

Distributed by CELESTY LLC

3970 NW 167TH ST. MIAMI GARDENS,

FL 33054 - USA

info@celesty.com

(FOR SENSITIVE SKIN)

Protects sensitive skin against UVA rays and acts against free radical damage that may occur because of sun rays.